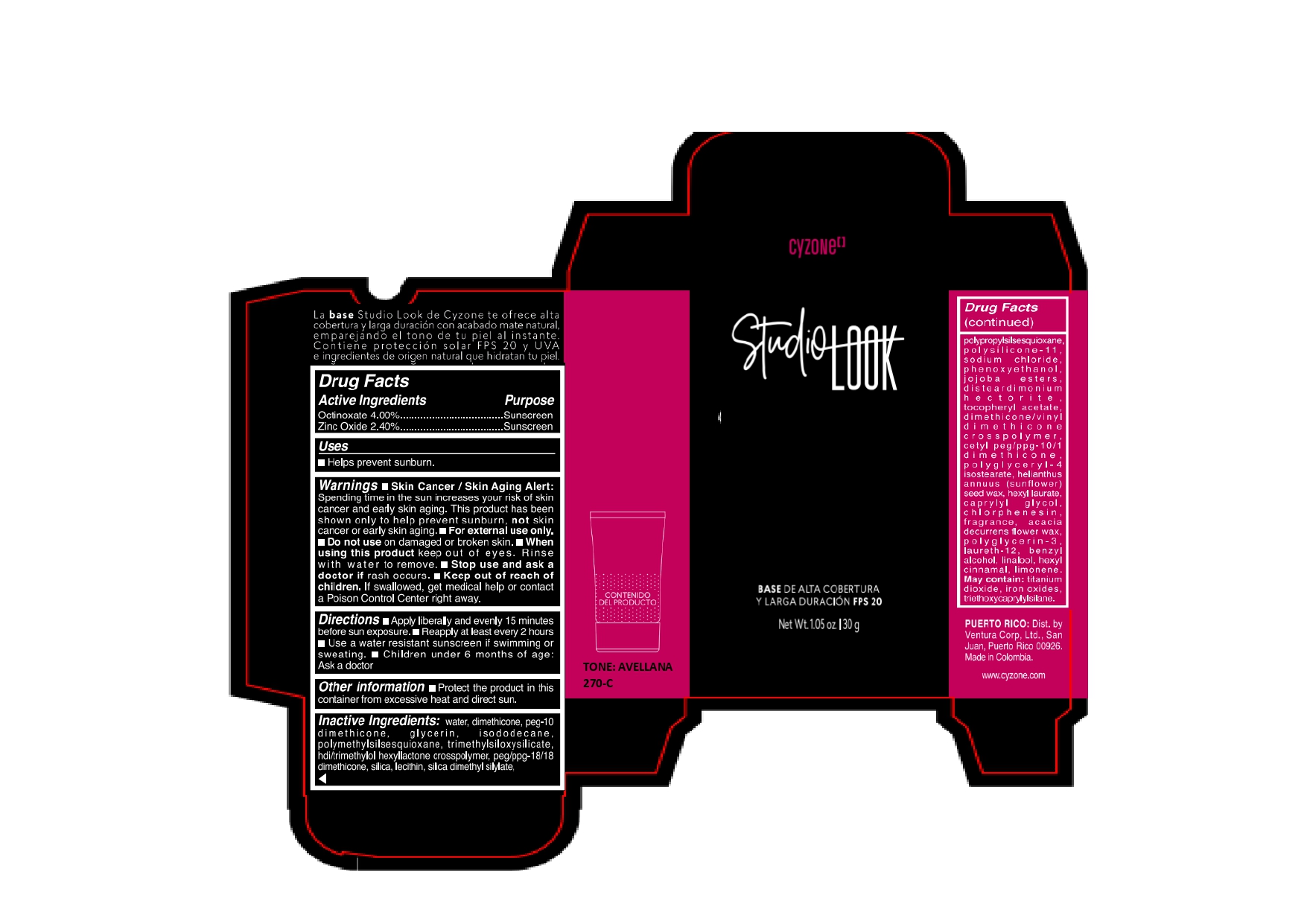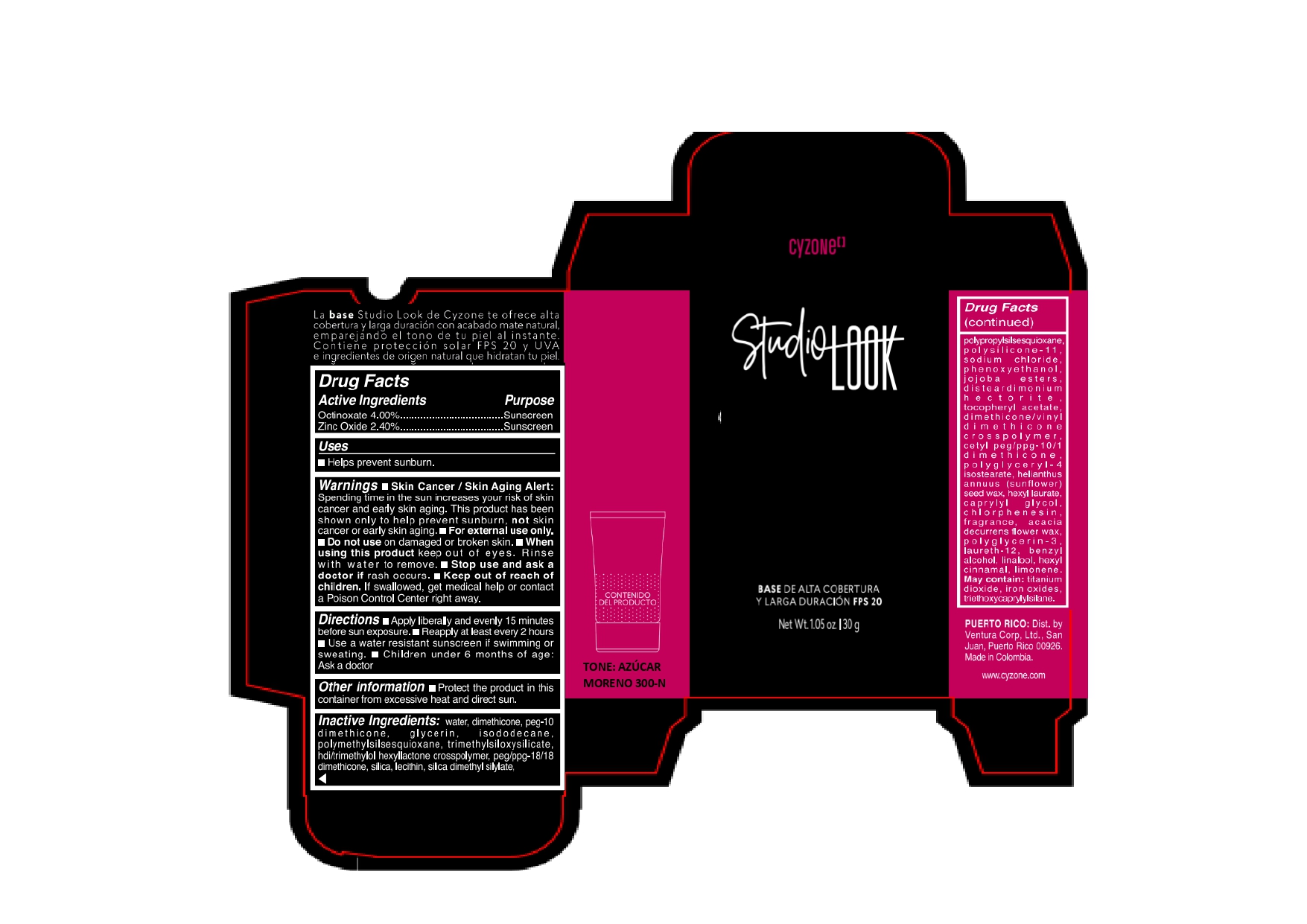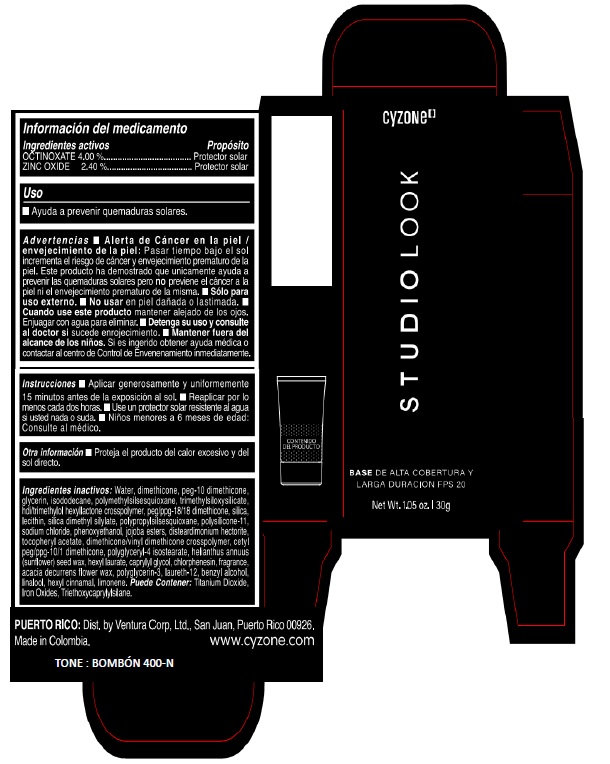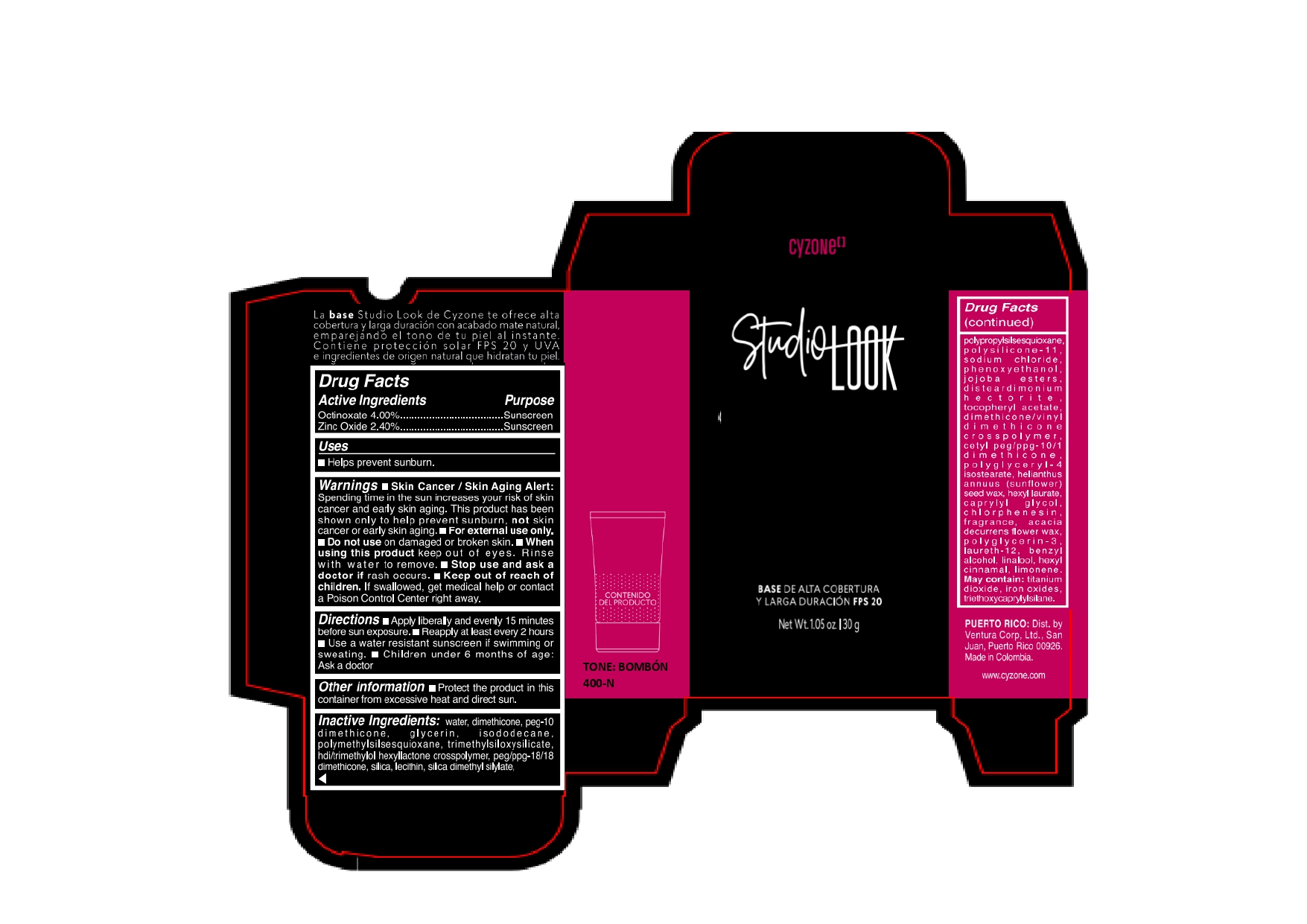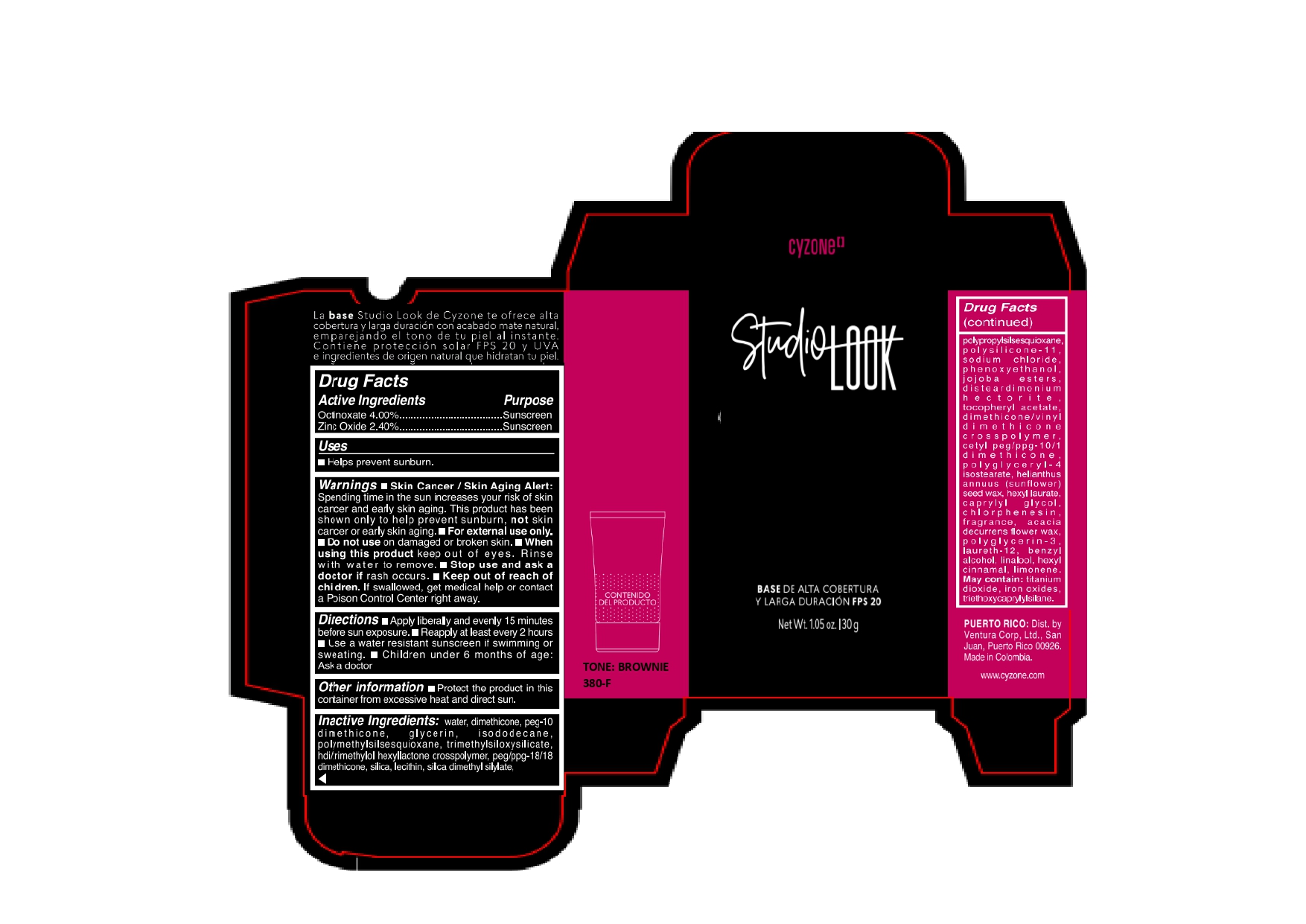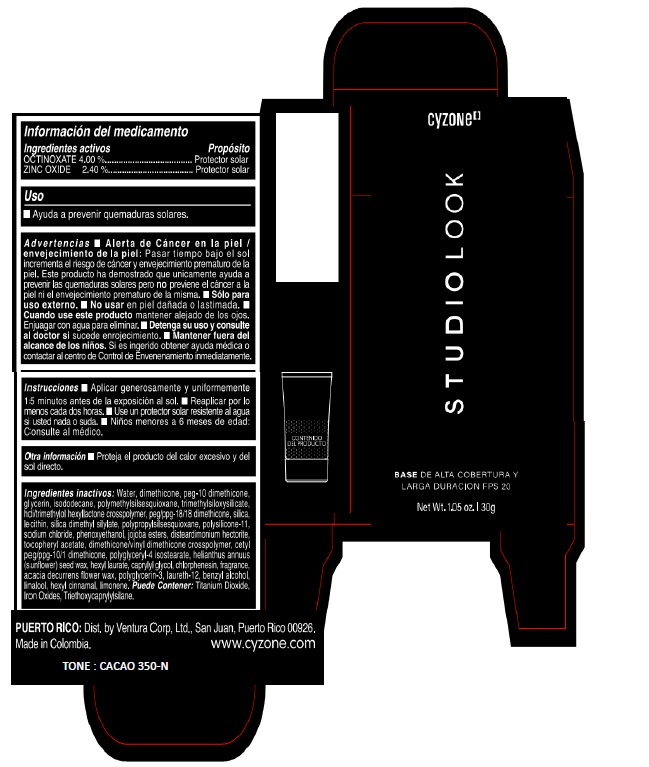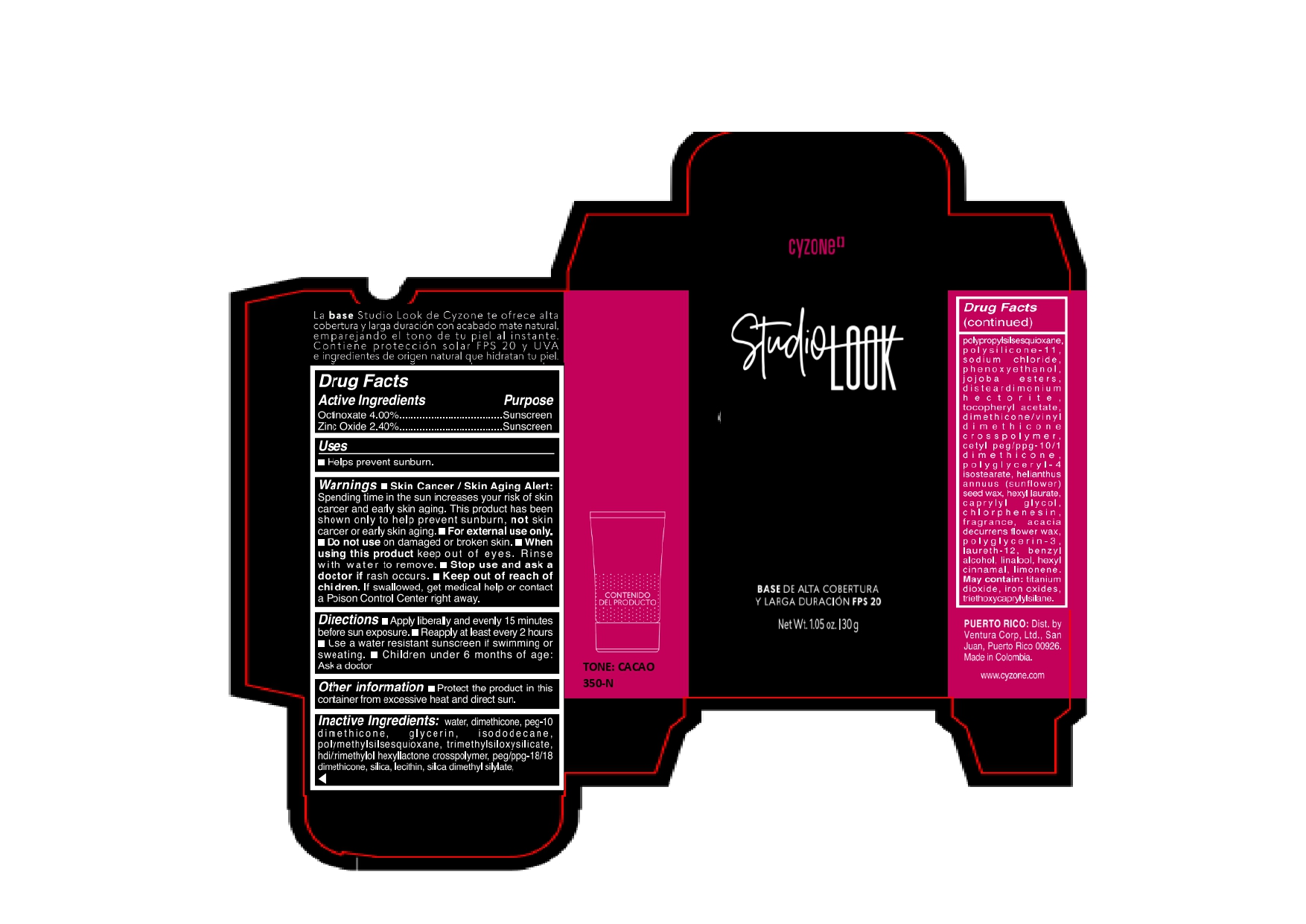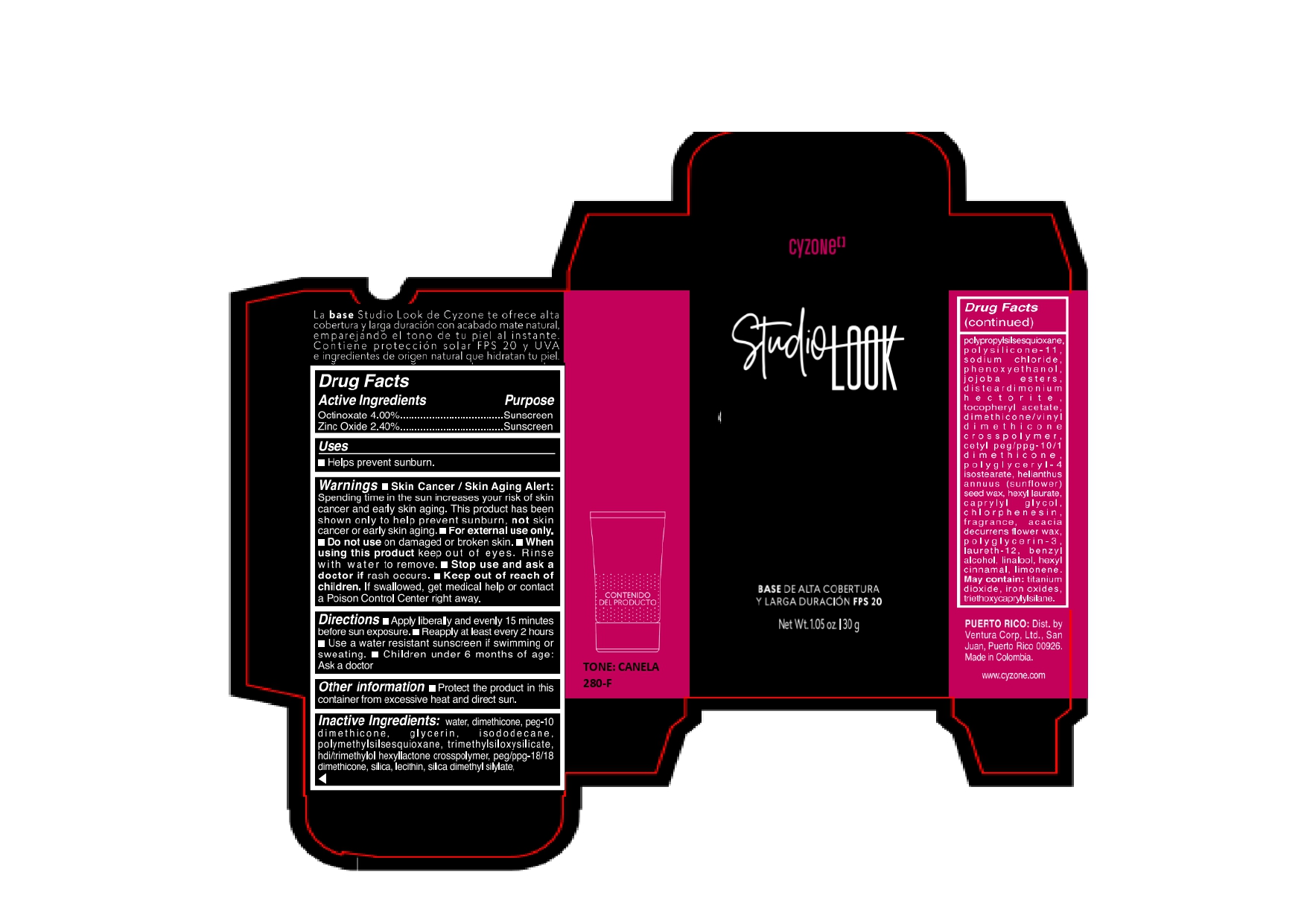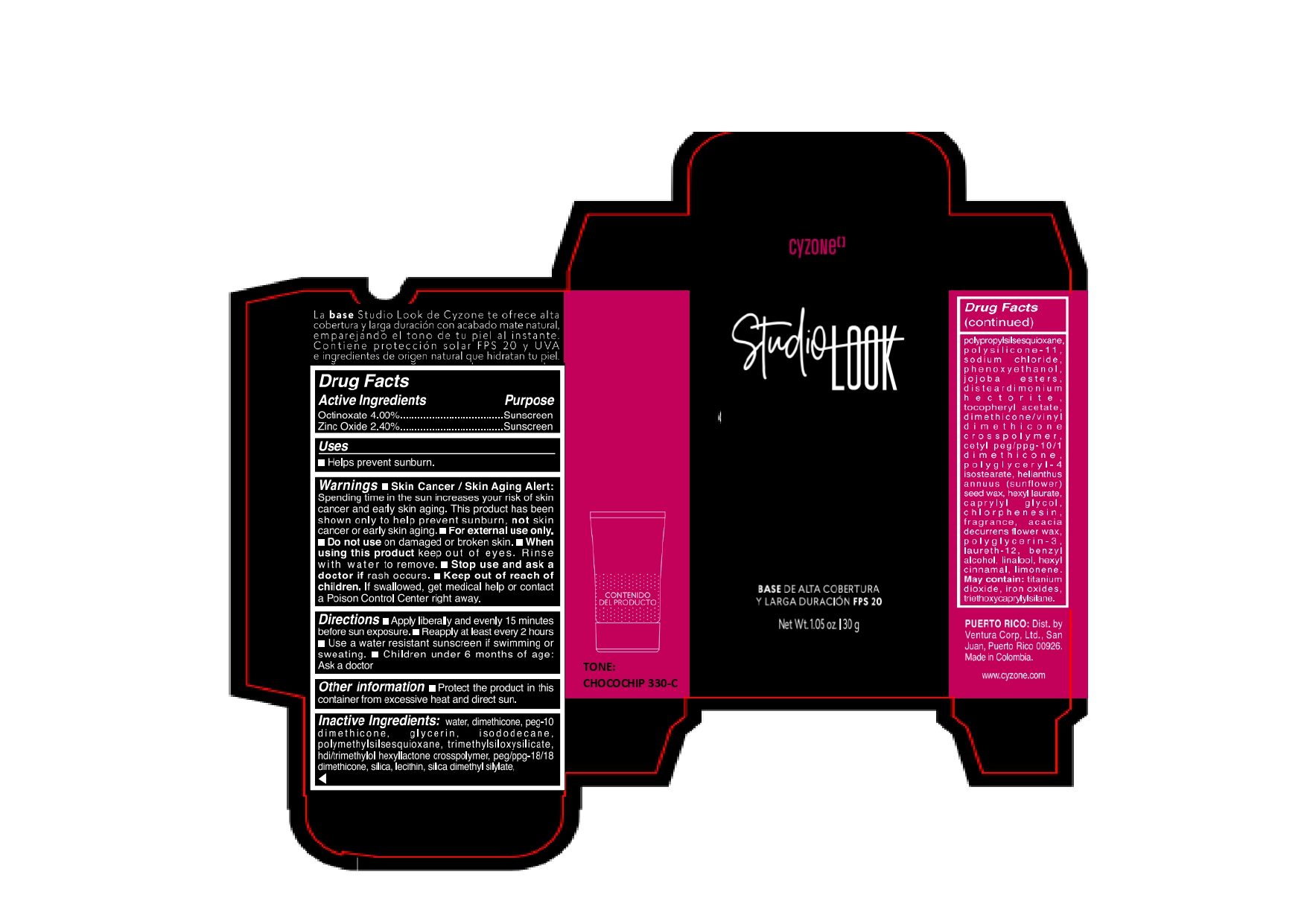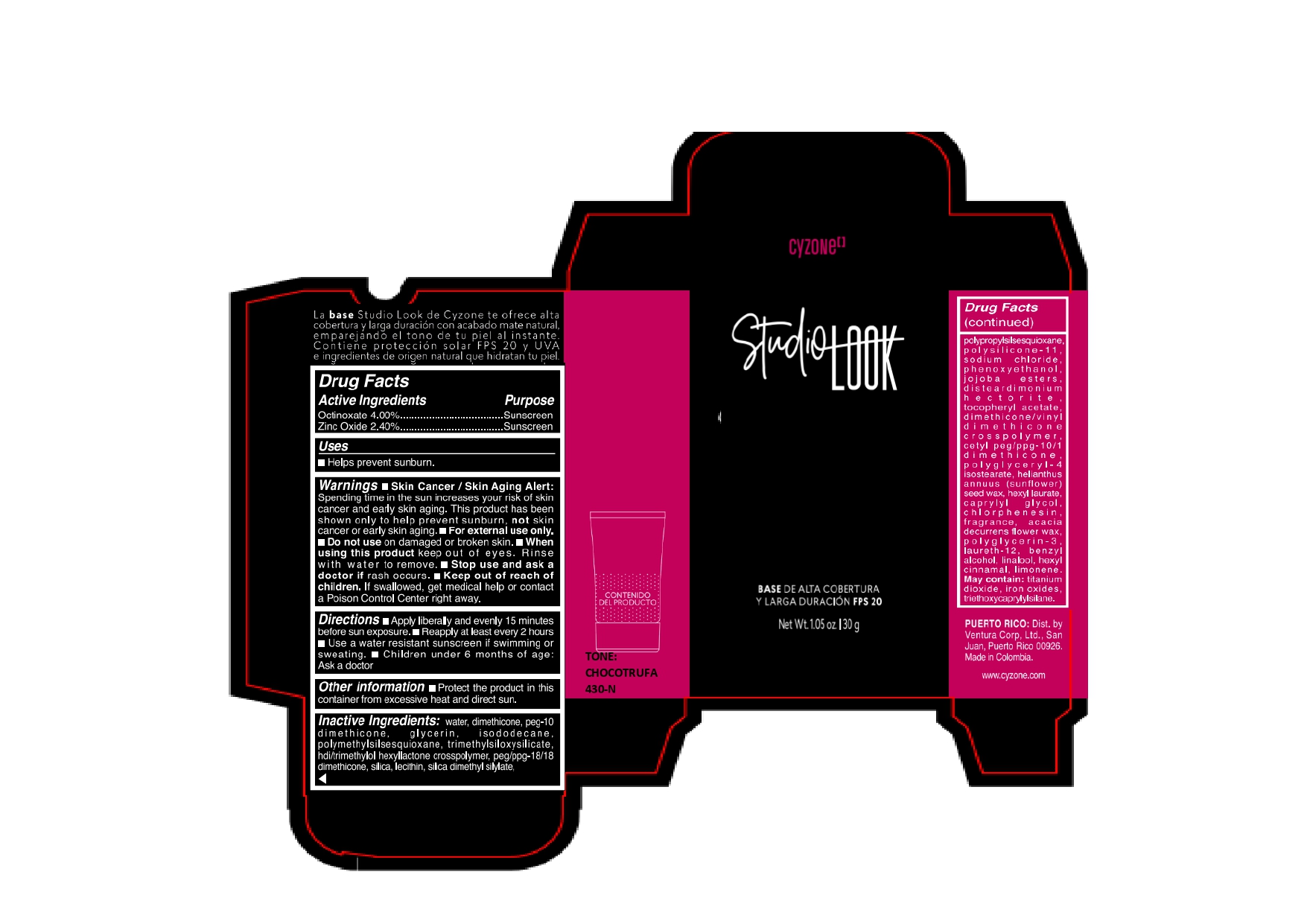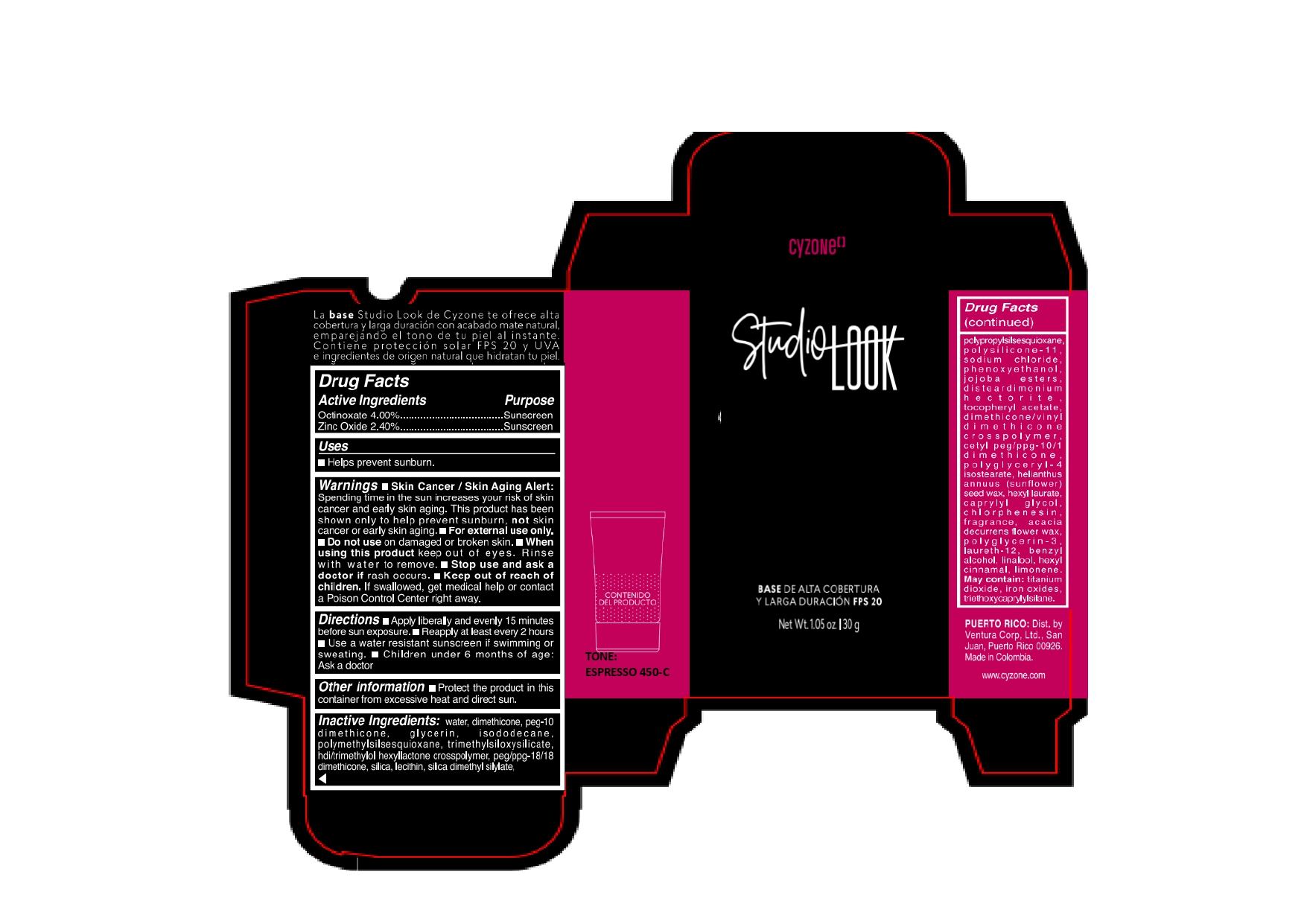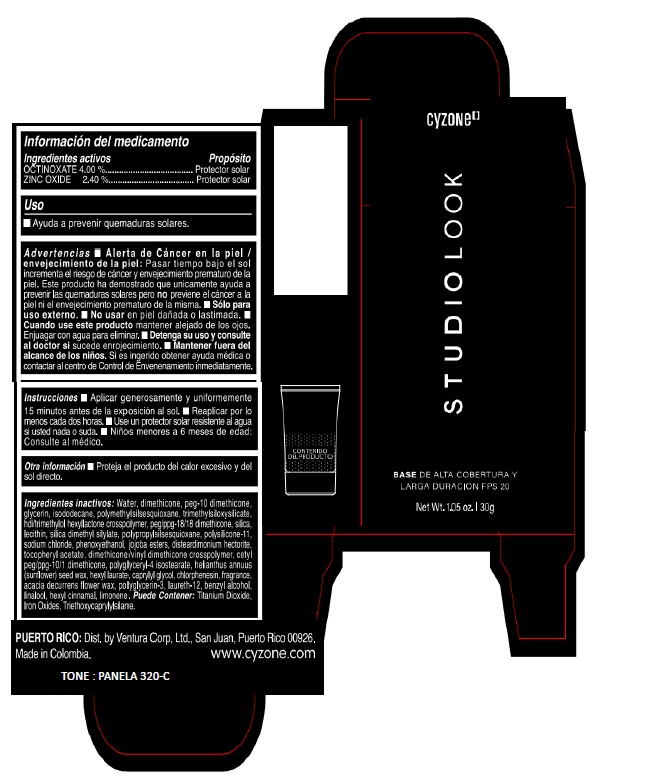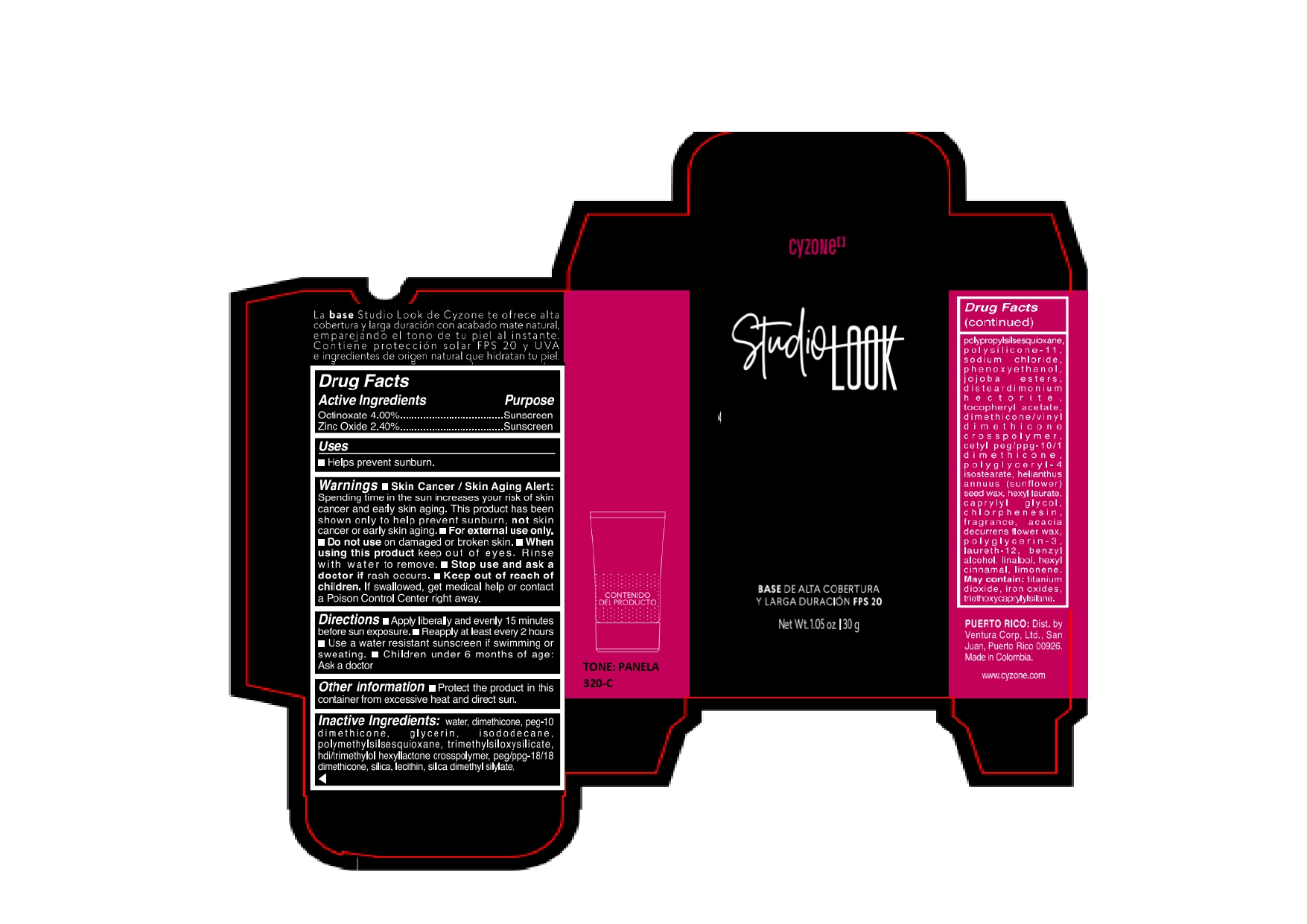 DRUG LABEL: CYZONE STUDIO LOOK BASE DE ALTA COBERTURA Y LARGA DURACION FPS 20 CANELA 280-F
NDC: 14141-034 | Form: EMULSION
Manufacturer: BEL STAR S A
Category: otc | Type: HUMAN OTC DRUG LABEL
Date: 20250221

ACTIVE INGREDIENTS: OCTINOXATE 40 mg/1 g; ZINC OXIDE 24 mg/1 g
INACTIVE INGREDIENTS: SILICA DIMETHYL SILYLATE; TRIMETHYLSILOXYSILICATE (M/Q 0.8-1.0); DIMETHICONE/VINYL DIMETHICONE CROSSPOLYMER (SOFT PARTICLE); JOJOBA OIL, RANDOMIZED; HELIANTHUS ANNUUS SEED WAX; ACACIA DECURRENS FLOWER WAX; GLYCERIN; FERROSOFERRIC OXIDE; PROPYLSILSESQUIOXANE, HYDROGEN TERMINATED; DISTEARDIMONIUM HECTORITE; HEXYL LAURATE; BENZYL ALCOHOL; FERRIC OXIDE YELLOW; PHENOXYETHANOL; DIMETHICONE; POLYMETHYLSILSESQUIOXANE (4.5 MICRONS); POLYGLYCERYL-4 ISOSTEARATE; CAPRYLYL GLYCOL; .ALPHA.-TOCOPHEROL ACETATE; LINALOOL, (+/-)-; LIMONENE, (+/-)-; FERRIC OXIDE RED; SILICON DIOXIDE; PEG/PPG-18/18 DIMETHICONE; HEXAMETHYLENE DIISOCYANATE/TRIMETHYLOL HEXYLLACTONE CROSSPOLYMER; SODIUM CHLORIDE; TITANIUM DIOXIDE; WATER; PEG-10 DIMETHICONE (600 CST); ISODODECANE; LECITHIN, SOYBEAN; POLYGLYCERIN-3; LAURETH-12; .ALPHA.-HEXYLCINNAMALDEHYDE; CETYL PEG/PPG-10/1 DIMETHICONE (HLB 5); CHLORPHENESIN; TRIETHOXYCAPRYLYLSILANE

CYZONE STUDIO LOOK BASE DE ALTA COBERTURA Y LARGA DURACION FPS 20

Active Ingredients

Octinoxate 4.00%

Zinc Oxide 2.40%

Purpose

Sunscreen

Uses

- Helps prevent sunburn.

Warnings

- Skin Cancer/Skin Aging Alert: Spending time in the sun increases your risk of skin cancer and early skin aging. This product has been shown only to help prevent sunburn, not skin cancer or early skin aging.
- For external use only.

Do not use

on damaged or broken skin.

When using this product

keep out of eyes. Rinse with water to remove.

Stop use and ask a doctor if

rash occurs.

Keep out of reach of children.

If swallowed, get medical help or contact a Poison Control Center right away.

Directions

- Apply liberally and evenly 15 minutes before sun exposure.
- Reapply at least every 2 hours.
- Use a water resistant sunscreen if swimming or sweating.
- Children under 6 months of age: Ask a doctor.

Other information

- Protect the product in this container from excessive heat and direct sun.

Inactive Ingredients:

water, dimethicone, peg-10 dimethicone, glycerin, isododecane, polymethylsilsesquioxane, trimethylsiloxysilicate, hdi/trimethylol hexyllactone crosspolymer, peg/ppg-18/18 dimethicone, silica, lecithin, silica dimethyl silylate, polypropylsilsesquioxane, polysilicone-11, sodium chloride, phenoxyethanol, jojoba esters, disteardimonium hectorite, tocopheryl acetate, dimethicone/vinyl dimethicone crosspolymer, cetyl peg/ppg-10/1 dimethicone, polyglyceryl-4 isostearate, helianthus annuus (sunflower) seed wax, hexyl laurate, caprylyl glycol, chlorphenesin, fragrance, acacia decurrens flower wax, polyglycerin-3, laureth-12, benzyl alcohol, linalool, hexyl cinnamal, limonene. May contain: titanium dioxide, iron oxides, triethoxycaprylylsilane.

Company Information

PUERTO RICO: Dist. by Ventura Corp, Ltd., San Juan, Puerto Rico 00926.

Made in Colombia.

www.cyzone.com